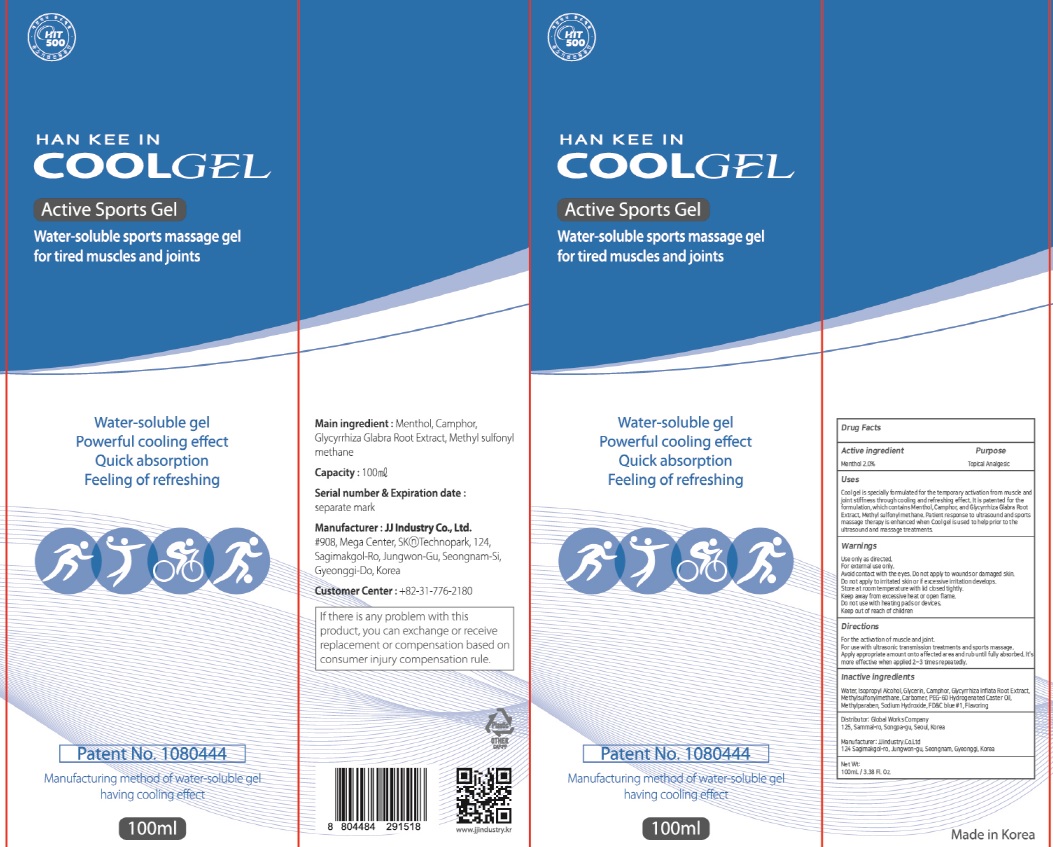 DRUG LABEL: HAN KEE IN COOL
NDC: 74353-010 | Form: GEL
Manufacturer: Globalworkscompany. Co., Ltd.
Category: otc | Type: HUMAN OTC DRUG LABEL
Date: 20200402

ACTIVE INGREDIENTS: Menthol 2.0 g/100 mL
INACTIVE INGREDIENTS: Water; Isopropyl Alcohol; Glycerin

ACTIVE INGREDIENT

Active ingredients: Menthol 2.0%

INACTIVE INGREDIENT

Inactive ingredients:

Water, Isopropyl Alcohol, Glycerin, Camphor, Glycyrrhiza Inflata Root Extract, Methylsulfonylmethane, Carbomer, PEG-60 Hydrogenated Caster Oil, Methylparaben, Sodium Hydroxide, FD&C blue #1, Flavoring

PURPOSE

Purpose: Topical Analgesic

WARNINGS

Use only as directed.
For external use only.
Avoid contact with the eyes. Do not apply to wounds or damaged skin.
Do not apply to irritated skin or if excessive irritation develops.
Store at room temperature with lid closed tightly.
Keep away from excessive heat or open flame.
Do not use with heating pads or devices.
Keep out of reach of children

KEEP OUT OF REACH OF CHILDREN

Uses

Cool gel is specially formulated for the temporary activation from muscle and joint stiffness through cooling and refreshing effect. It is patented for the formulation, which contains Menthol, Camphor, and Glycyrrhiza Glabra Root Extract, Methyl sulfonyl methane. Patient response to ultrasound and sports massage therapy is enhanced when Cool gel is used to help prior to the ultrasound and massage treatments.

Directions

For the activation of muscle and joint.
For use with ultrasonic transmission treatments and sports massage.
Apply appropriate amount onto affected area and rub until fully absorbed. It's more effective when applied 2~3 times repeatedly.